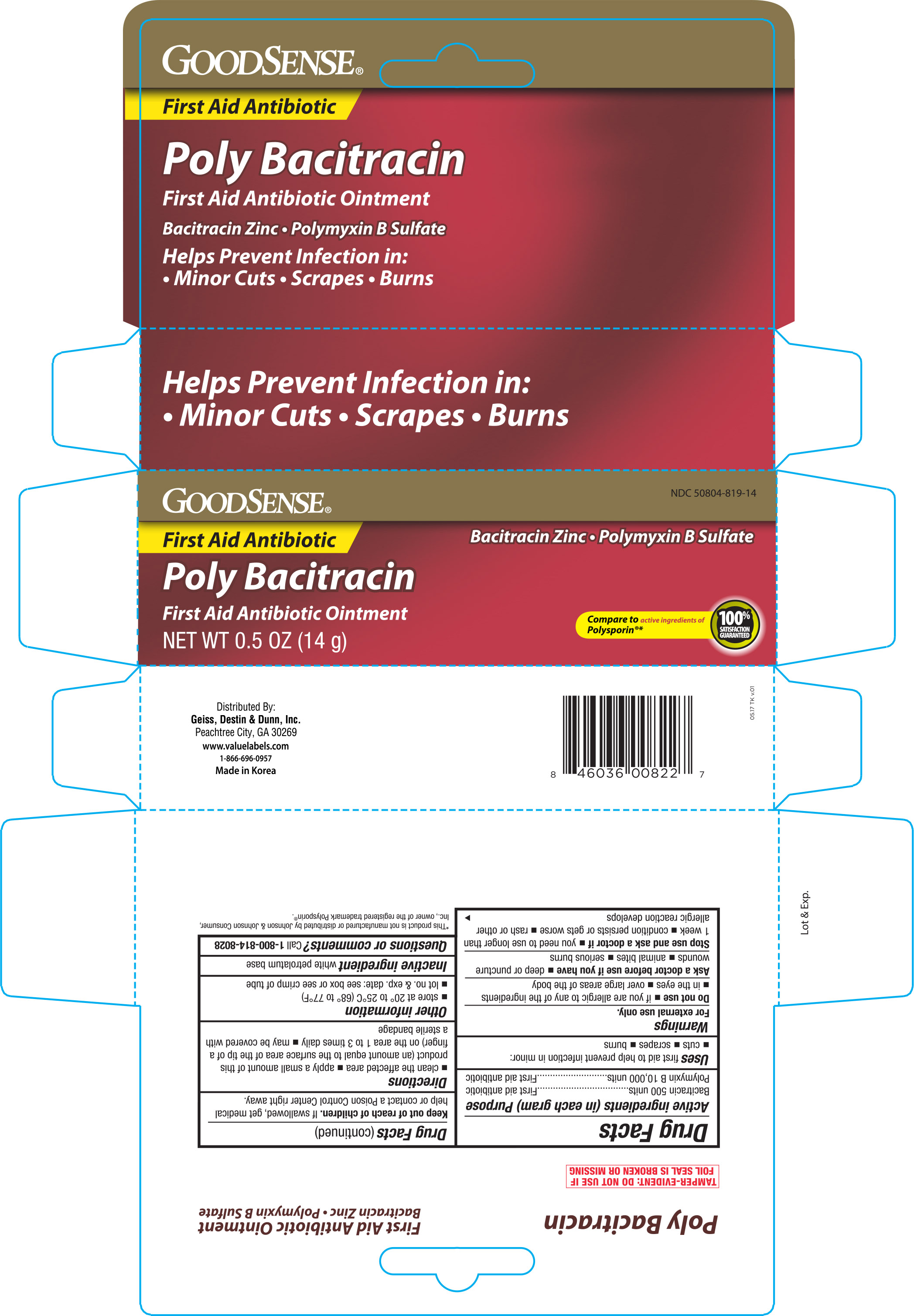 DRUG LABEL: Goodsense First Aid Antibiotic
NDC: 50804-819 | Form: OINTMENT
Manufacturer: Geiss, Destin & Dunn, Inc
Category: otc | Type: HUMAN OTC DRUG LABEL
Date: 20170815

ACTIVE INGREDIENTS: POLYMYXIN B SULFATE 10000 [USP'U]/1 g; BACITRACIN ZINC 500 [USP'U]/1 g
INACTIVE INGREDIENTS: PETROLATUM

Active ingredients (in each gram) Purpose

Bacitracin 500 units..................First aid antibiotic

Polymyxin B 10,000 units..........First aid antibiotic

PURPOSE

Uses first aid to help prevent infection in minor:

- cuts
- scrapes
- burns

Warnings

For external use only.

Do not use

- if you are allergic to any of the ingredients
- in the eyes
- over large areas of the body

Ask a doctor before use if you have

- deep or puncture wounds
- animal bites
- serious burns

Stop use and ask a doctor if

- you need to use longer than 1 week
- condition persists or gets worse
- rash or other allergic reaction develops

Keep out of reach of children.

If swallowed, get medical help or contact a Poison Control Center right away.

Directions

- clean the affected area
- apply a small amount of this product (an amount equal to the surface area of the tip of a finger) on the area 1 to 3 times daily
- may be covered with a sterile bandage

Other information

- store at 20° to 25°C (68° to 77°F)
- lot no. & exp. date: see box or see crimp of tube

Inactive ingredient

white petrolatum base

DOSAGE AND ADMINISTRATION

Distributed By:

Geiss, Destin & Dunn, Inc.

Peachtree City, GA 30269

www.valuelabels.com

1-866-696-0957

Made in Korea